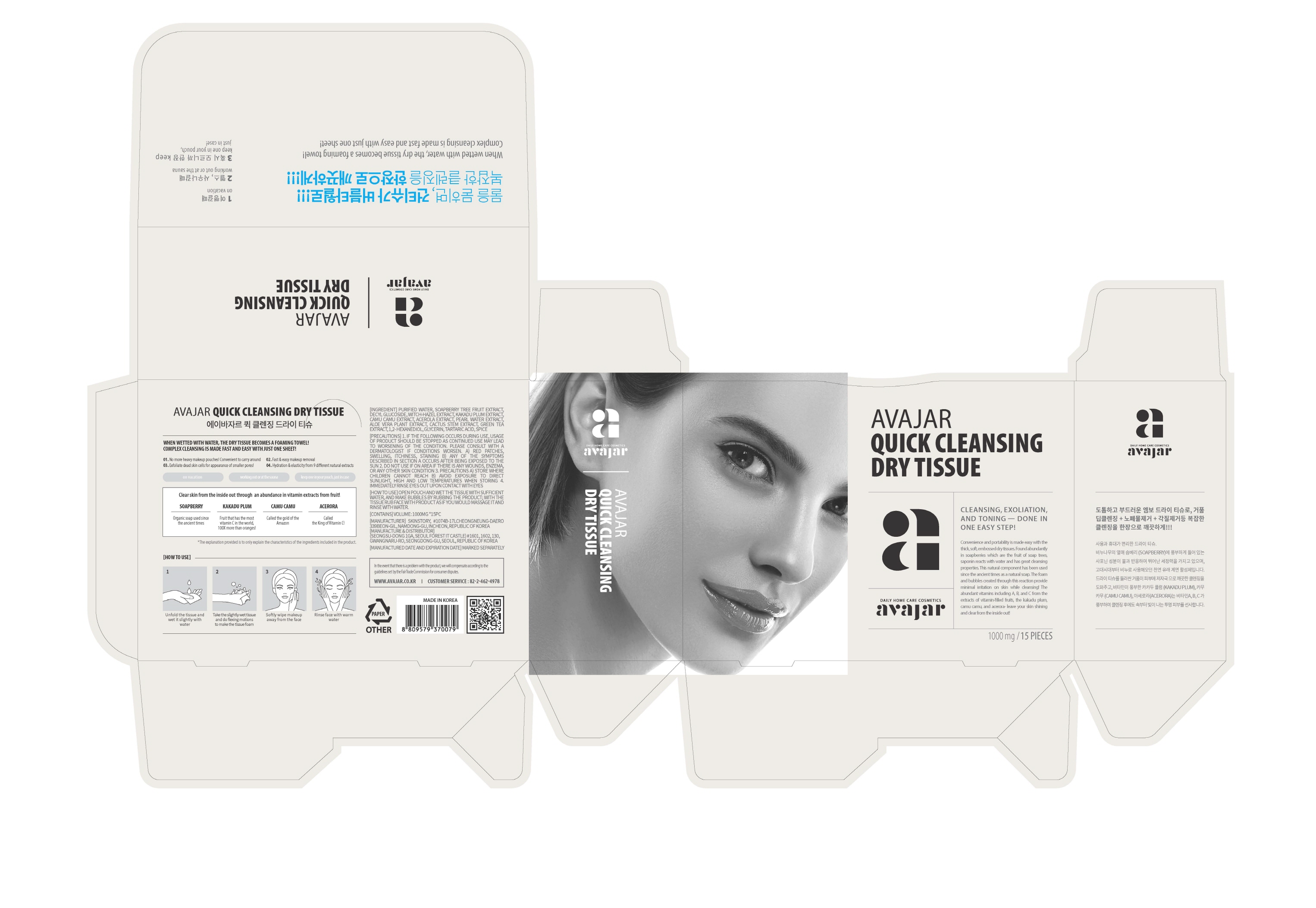 DRUG LABEL: QUICK CLEANSING DRY TISSUE
NDC: 71224-0006 | Form: LIQUID
Manufacturer: AVAJAR CO LTD
Category: otc | Type: HUMAN OTC DRUG LABEL
Date: 20180710

ACTIVE INGREDIENTS: GLYCERIN 0.8 g/100 g
INACTIVE INGREDIENTS: WATER; ALOE VERA LEAF; TARTARIC ACID

Drug Facts

ACTIVE INGREDIENT

Glycerin

INACTIVE INGREDIENT

Water, Hamamelis Virginiana (Witch Hazel) extract, Terminalia Ferdinandiana Fruit extract, Malpighia Emarginata (Acerola) Fruit extract, etc.

PURPOSE

Skin protectant: Cleansing

keep out of reach of the children

INDICATIONS AND USAGE

1. Unfold the tissue and wet it slightly with water.

2. Take the slightly wet tissue and do flexing motions to make the tissue foam.

3. Softly wipe makeup away from the face.

4. Rinse face with warm water.

DOSAGE AND ADMINISTRATION

for external use only

WARNINGS

1. If the following symptoms occur after product use, stop using the product immediately and consult a dermatologist (continuous use can exacerbate the symptoms).
1) Occurrence of red spots, swelling, itchiness, and other skin irritation
2) If the symptoms above occur after the application area is exposed to direct sunlight
2. Do not use on open wounds, eczema, and other skin irritations
3. Precaution for Storage and Handling
1) Close the lid after use
2) Keep out of reach of infants and children
3) Do not to store in a place with high/low temperature and exposed to direct sunlight